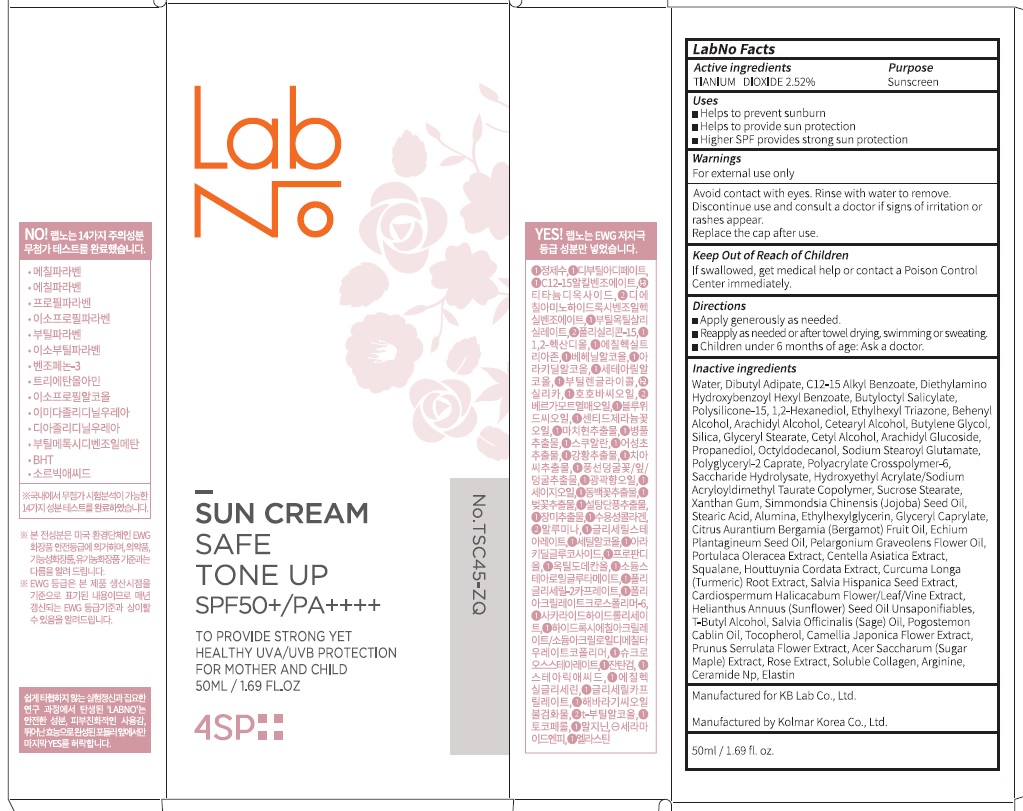 DRUG LABEL: LabNo 4SP Safe Tone Up Sun
NDC: 71497-010 | Form: CREAM
Manufacturer: KB Lab Co., Ltd.
Category: otc | Type: HUMAN OTC DRUG LABEL
Date: 20170711

ACTIVE INGREDIENTS: Titanium Dioxide 1.26 g/50 mL
INACTIVE INGREDIENTS: Water; Dibutyl Adipate

ACTIVE INGREDIENT

Active ingredients: Titanium Dioxide 2.52%

INACTIVE INGREDIENT

Inactive ingredients: Water, Dibutyl Adipate, C12-15 Alkyl Benzoate, Diethylamino Hydroxybenzoyl Hexyl Benzoate, Butyloctyl Salicylate, Polysilicone-15, 1,2-Hexanediol, Ethylhexyl Triazone, Behenyl Alcohol, Arachidyl Alcohol, Cetearyl Alcohol, Butylene Glycol, Silica, Glyceryl Stearate, Cetyl Alcohol, Arachidyl Glucoside, Propanediol, Octyldodecanol, Sodium Stearoyl Glutamate, Polyglyceryl-2 Caprate, Polyacrylate Crosspolymer-6, Saccharide Hydrolysate, Hydroxyethyl Acrylate/Sodium Acryloyldimethyl Taurate Copolymer, Sucrose Stearate, Xanthan Gum, Simmondsia Chinensis (Jojoba) Seed Oil, Stearic Acid, Alumina, Ethylhexylglycerin, Glyceryl Caprylate, Citrus Aurantium Bergamia (Bergamot) Fruit Oil, Echium Plantagineum Seed Oil, Pelargonium Graveolens Flower Oil, Portulaca Oleracea Extract, Centella Asiatica Extract, Squalane, Houttuynia Cordata Extract, Curcuma Longa (Turmeric) Root Extract, Salvia Hispanica Seed Extract, Cardiospermum Halicacabum Flower/Leaf/Vine Extract, Helianthus Annuus (Sunflower) Seed Oil Unsaponifiables, T-Butyl Alcohol, Salvia Officinalis (Sage) Oil, Pogostemon Cablin Oil, Tocopherol, Camellia Japonica Flower Extract, Prunus Serrulata Flower Extract, Acer Saccharum (Sugar Maple) Extract, Rose Extract, Soluble Collagen, Arginine, Ceramide Np, Elastin

PURPOSE

Purpose: Sunscreen

WARNINGS

Warnings: For external use only Avoid contact with eyes. Rinse with water to remove. Discontinue use and consult a doctor if signs of irritation or rashes appear. Replace the cap after use.

Keep Out of Reach of Children: If swallowed, get medical help or contact a Poison Control Center immediately.

DESCRIPTION

Uses:

- Helps to prevent sunburn

- Helps to provide sun protection

- Higher SPF provides strong sun protection

Directions:

- Apply generously as needed.

- Reapply as needed or after towel drying, swimming or sweating.

- Children under 6 months of age: Ask a doctor.